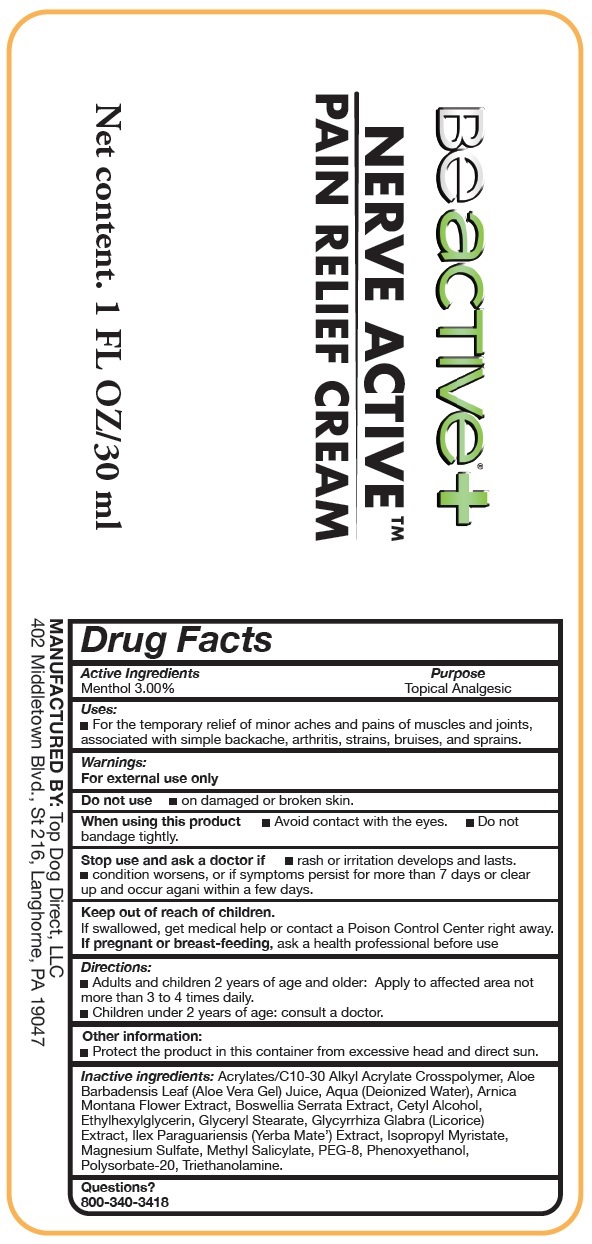 DRUG LABEL: NERVE ACTIVE Pain Relief Cream
NDC: 83690-422 | Form: CREAM
Manufacturer: TOP DOG DIRECT, LLC
Category: otc | Type: HUMAN OTC DRUG LABEL
Date: 20231111

ACTIVE INGREDIENTS: MENTHOL 30 mg/1 mL
INACTIVE INGREDIENTS: ALOE VERA LEAF; WATER; ARNICA MONTANA FLOWER; INDIAN FRANKINCENSE; CETYL ALCOHOL; ETHYLHEXYLGLYCERIN; GLYCERYL MONOSTEARATE; GLYCYRRHIZA GLABRA; ILEX PARAGUARIENSIS LEAF; ISOPROPYL MYRISTATE; MAGNESIUM SULFATE, UNSPECIFIED FORM; METHYL SALICYLATE; POLYETHYLENE GLYCOL 400; PHENOXYETHANOL; POLYSORBATE 20; TROLAMINE

NERVE ACTIVE Pain Relief Cream

Active Ingredients

Menthol 3.00%

Purpose

Topical Analgesic

Uses:

- For the temporary relief of minor aches and pains of muscles and joints, associated with simple backache, arthritis, strains, bruises, and sprains.

Warnings:

For external use only

Do not use

- on damaged or broken skin.

When using this product

- Avoid contact with the eyes.
- Do not bandage tightly.

Stop use and ask a doctor if

- rash or irritation develops and lasts.
- condition worsens, or if symptoms persist for more than 7 days or clear up and occur agani within a few days.

Keep out of reach of children.

If swallowed, get medical help or contact a Poison Control Center right away.

If pregnant or breast-feeding,

ask a health professional before use

Directions:

- Adults and children 2 years of age and older: Apply to affected area not more than 3 to 4 times daily.
- Children under 2 years of age: consult a doctor.

Other information:

- Protect the product in this container from excessive head and direct sun.

Inactive ingredients:

Acrylates/C10-30 Alkyl Acrylate Crosspolymer, Aloe Barbadensis Leaf (Aloe Vera Gel) Juice, Aqua (Deionized Water), Arnica Montana Flower Extract, Boswellia Serrata Extract, Cetyl Alcohol, Ethylhexylglycerin, Glyceryl Stearate, Glycyrrhiza Glabra (Licorice) Extract, Ilex Paraguariensis (Yerba Mate’) Extract, Isopropyl Myristate, Magnesium Sulfate, Methyl Salicylate, PEG-8, Phenoxyethanol, Polysorbate-20, Triethanolamine.

Questions?

800-340-3418